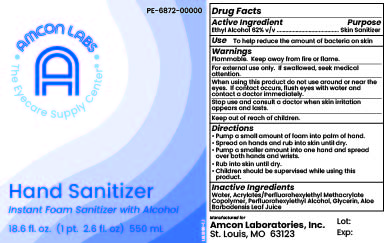 DRUG LABEL: Amcon Labs Hand Sanitizer Instant Foam Sanitizer with Alcohol
NDC: 51801-366 | Form: SOLUTION
Manufacturer: Nomax, Inc.
Category: otc | Type: HUMAN OTC DRUG LABEL
Date: 20231120

ACTIVE INGREDIENTS: ALCOHOL 620 mL/1 L
INACTIVE INGREDIENTS: WATER; 2-(PERFLUOROHEXYL)ETHANOL; BUTYL ACRYLATE/METHYL METHACRYLATE/PERFLUOROHEXYLETHYL METHACRYLATE COPOLYMER (SALUS AF); GLYCERIN; ALOE VERA LEAF

Amcon Labs Hand Sanitizer Instant Foam Sanitizer with Alcohol

Active Ingredient

Ethyl Alcohol 62% v/v

Purpose

Skin Sanitizer

Use

To help reduce the amount of bacteria on skin

Warnings

Flammable. Keep away from fire or flame.

For external use only. If swallowed, seek medical attention.

When using this product do not use around or near the eyes. If contact occurs, flush eyes with water and contact a doctor immediately.

Stop use and consult a doctor when skin irritation appears and lasts.

Keep out of reach of children.

Directions

- Pump a small amount of foam into palm of hand.
- Spread on hands and rub into skin until dry.
- Pump a smaller amount into one hand and spread over both hands and wrists.
- Rub into skin until dry.
- Children should be supervised while using this product.

Inactive Ingredients

Water, Acrylates/Perfluorohexylethyl Methacrylate Copolymer, Perfluorohexylethyl Alcohol, Glycerin, Aloe Barbadensis Leaf Juice